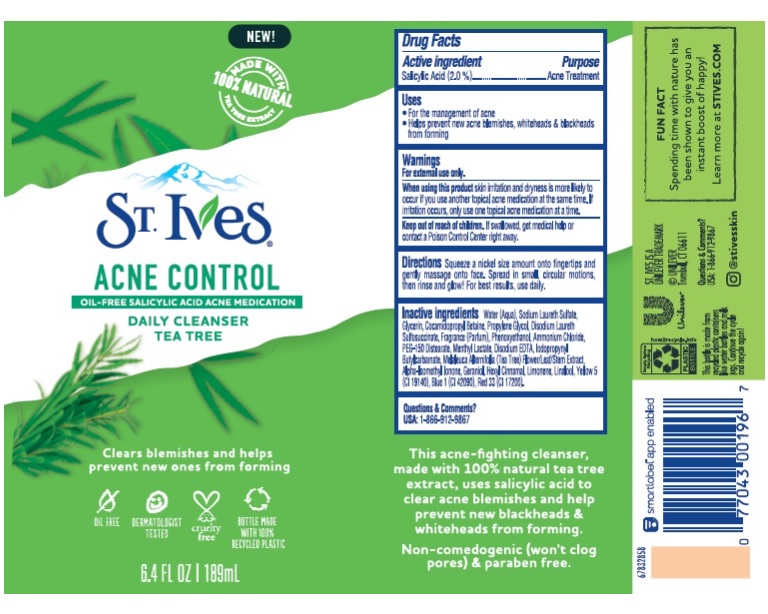 DRUG LABEL: St. Ives
NDC: 64942-1865 | Form: LOTION
Manufacturer: CONOPCO Inc. d/b/a Unilever
Category: otc | Type: HUMAN OTC DRUG LABEL
Date: 20241107

ACTIVE INGREDIENTS: SALICYLIC ACID 2 g/100 mL
INACTIVE INGREDIENTS: WATER; GLYCERIN; SODIUM LAURETH SULFATE; DISODIUM LAURETH SULFOSUCCINATE; COCAMIDOPROPYL BETAINE; PHENOXYETHANOL; AMMONIUM CHLORIDE; PEG-150 DISTEARATE; MENTHYL LACTATE, (-)-; MELALEUCA ALTERNIFOLIA FLOWERING TOP; FD&C BLUE NO. 1; PROPYLENE GLYCOL; GERANIOL; FD&C YELLOW NO. 5; EDETATE DISODIUM ANHYDROUS; IODOPROPYNYL BUTYLCARBAMATE; D&C RED NO. 33; ISOMETHYL-.ALPHA.-IONONE; .ALPHA.-HEXYLCINNAMALDEHYDE; LINALOOL, (+/-)-; LIMONENE, (+)-

St. Ives Solutions Acne Control Tea Tree Cleanser

Active ingredient

Salicylic Acid (2%)

Purpose

Acne Treatment

Uses

For the mangement of acne
Helps keep skin clear of new acne pimples and acne blemishes

Warnings

For external use only
When using this product s kin irritation and dryness is more likely to occur if you use another topical acne medication at the same time. If irritation occues, only use one topical acne medication at a time .

Keep out of reach of children
If swallowed, get medical help or contact a Poison Control Center right away.

Directions

Dispense a nickel size amount onto fingertips and gently massage onto face. Spread in small, circular motions, then rinse and glow! For best results, use daily.

Inactive ingredients

Water (Aqua), Sodium Laureth Sulfate, Glycerin, Cocamidopropyl Betaine, Propylene Glycol, Disodium Laureth Sulfosuccinate, Fragrance (Parfum), Phenoxyethanol, Ammonium Chloride, PEG-150 Distearate, Menthyl Lactate, Disodium EDTA, Iodopropynyl Butylcarbamate, Melaleuca Alternifolia (Tea Tree) Flower/Leaf/Stem Extract, Alpha-Isomethyl Ionone, Geraniol, Hexyl Cinnamal, Limonene, Linalool, Yellow 5 (CI 19140), Blue 1 (CI 42090), Red 33 (CI 17200),

Questions or comments?

USA: 1-866-912-9867